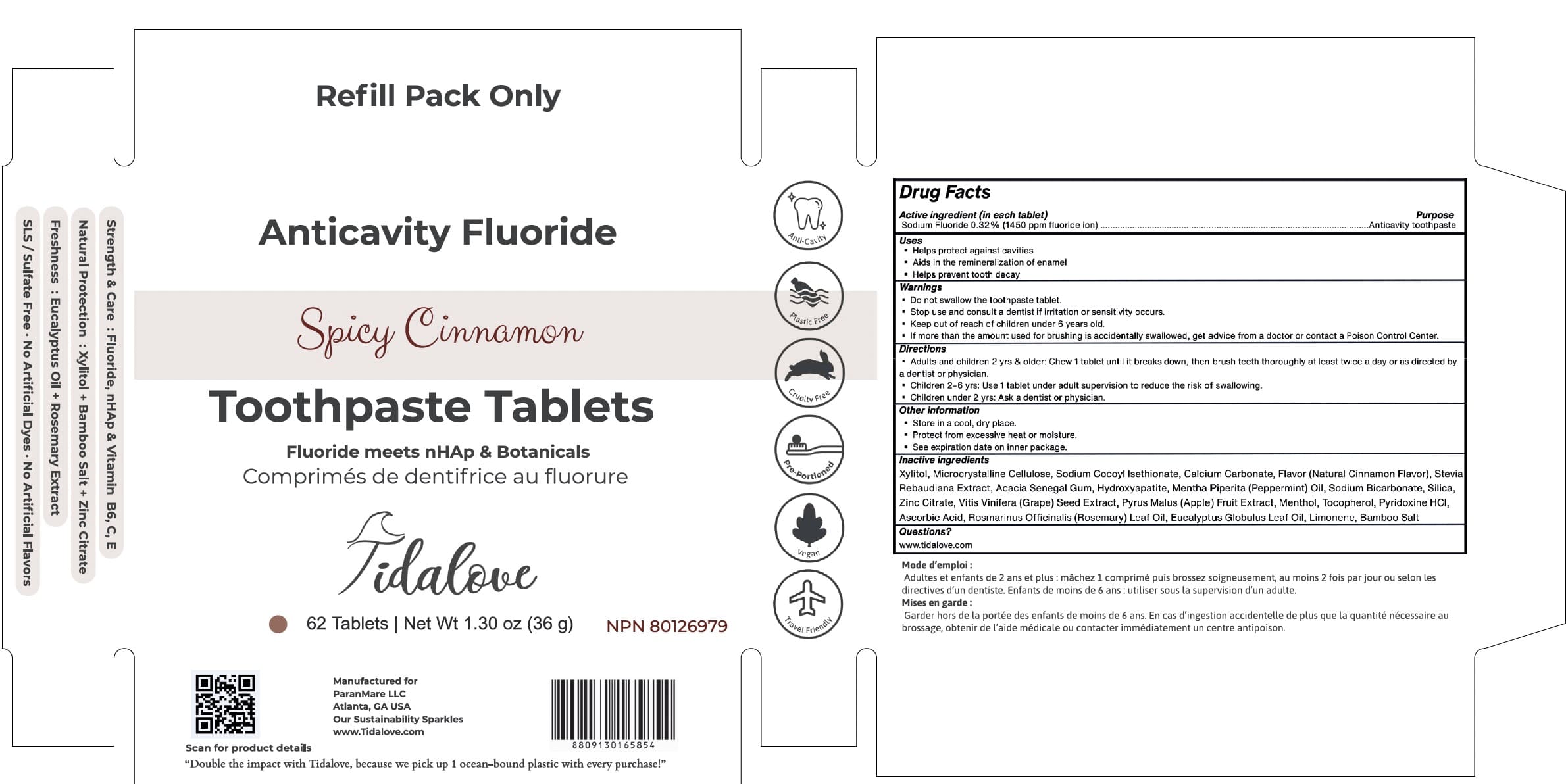 DRUG LABEL: Tidalove
NDC: 82756-223 | Form: TABLET, CHEWABLE
Manufacturer: Paranmare LLC
Category: otc | Type: HUMAN OTC DRUG LABEL
Date: 20251007

ACTIVE INGREDIENTS: SODIUM FLUORIDE 0.32 mg/1 1
INACTIVE INGREDIENTS: CINNAMON OIL; ASCORBIC ACID; LIMONENE, (+/-)-; SODIUM COCOYL ISETHIONATE; CALCIUM CARBONATE; SILICON DIOXIDE; SODIUM CHLORIDE; APPLE; ZINC CITRATE; STEVIOSIDE; XYLITOL; CELLULOSE, MICROCRYSTALLINE; MENTHOL; PYRIDOXINE HCL; ROSEMARY OIL; SODIUM BICARBONATE; VITIS VINIFERA SEED; TOCOPHEROL; TRIBASIC CALCIUM PHOSPHATE; PEPPERMINT OIL; ACACIA

Paranmare-Muyme Cinnamon2025

Active Ingredient(s)

Sodium Fluoride 0.32% 1450 ppm fluoride ion

Purpose

Anticavity

Use

Helps protect against cavities
Aids in the remineralization of enamel
Helps prevent tooth decay

Warnings

Do not swallow the toothpaste tablet.
Stop use and consult a dentist if irritation or sensitivity occurs.
Keep out of reach of children under 6 years old.
If more than the amount used for brushing is accidentally swallowed, get advice from a doctor or contact a Poison Control Center.

KEEP OUT OF REACH OF CHILDREN

If more than used for brushing is accidentally swallowed, get medical help or contact a Poison Control Center immediately.

Directions

- Adults and children 2 yrs & older: Chew 1 tablet until it breaks down, then brush teeth thoroughly at least twice a day or as directed by
  a dentist or physician.
  Children 2-6 yrs: Use 1 tablet under adult supervision to reduce the risk of swallowing.
  • Children under 2 yrs: Ask a dentist or physician.

Other information

Store in a cool, dry place.
Protect from excessive heat or moisture.
See expiration date on inner package.

Inactive ingredients

Xylitol, Microcrystalline Cellulose, Sodium Cocoyl Isethionate, Calcium Carbonate, Flavor (Natural Cinnamon Flavor), Stevia Rebaudiana Extract, Acacia Senegal Gum, Hydroxyapatite, Mentha Piperita (Peppermint) Oil, Sodium Bicarbonate, Silica, Zinc Citrate, Vitis Vinifera (Grape) Seed Extract, Pyrus Malus (Apple) Fruit Extract, Menthol, Tocopherol, Pyridoxine HCI,

Ascorbic Acid, Rosmarinus Officinalis (Rosemary) Leaf Oil, Eucalyptus Globulus Leaf Oil, Limonene, Bamboo Salt

QUESTIONS

www.tidalove.com